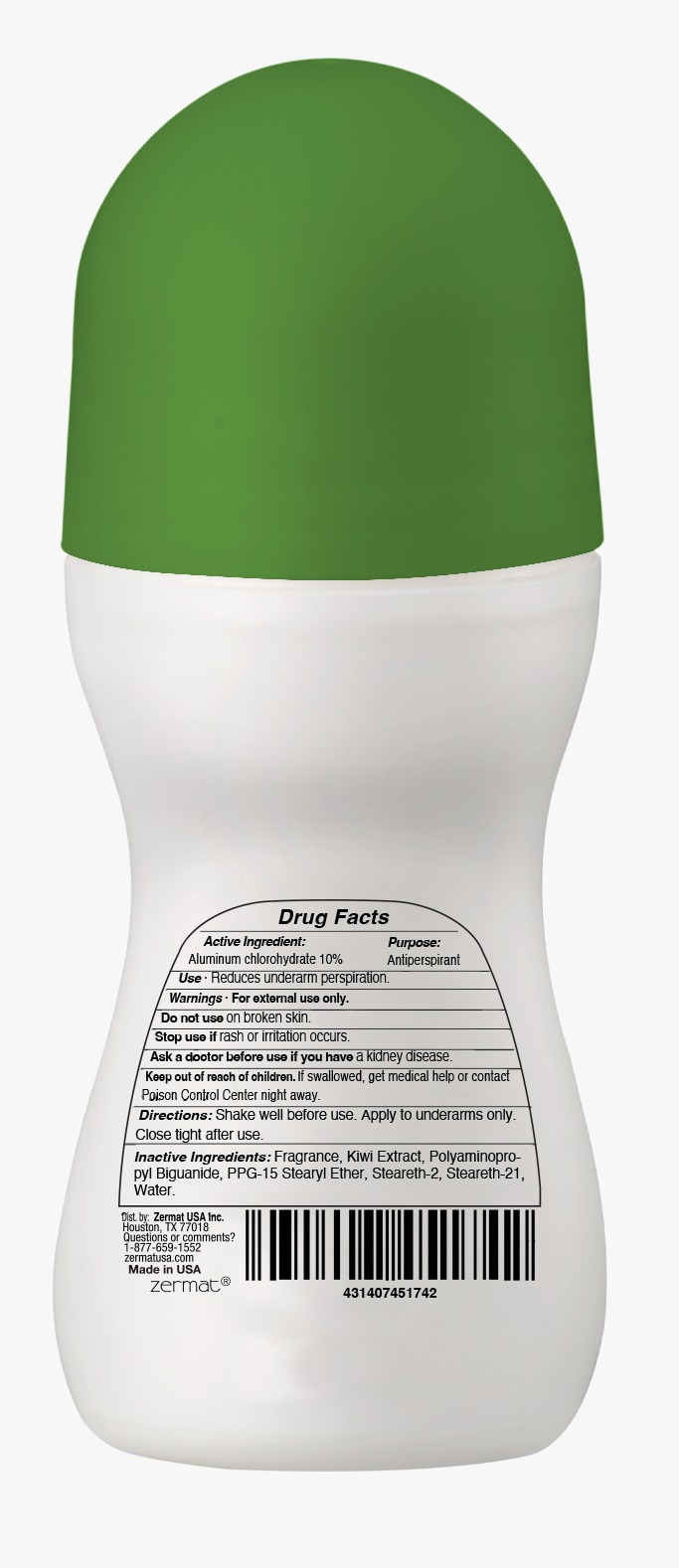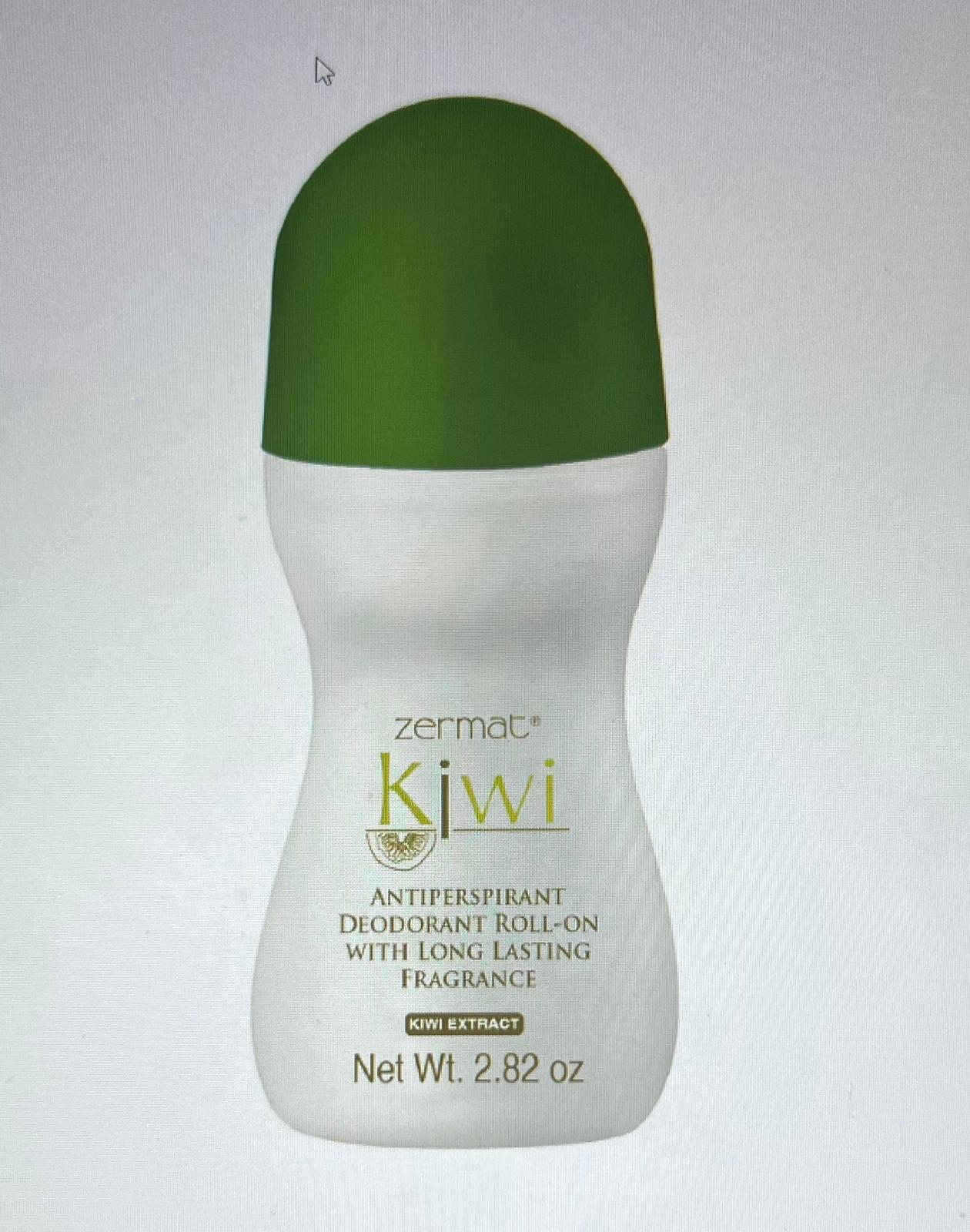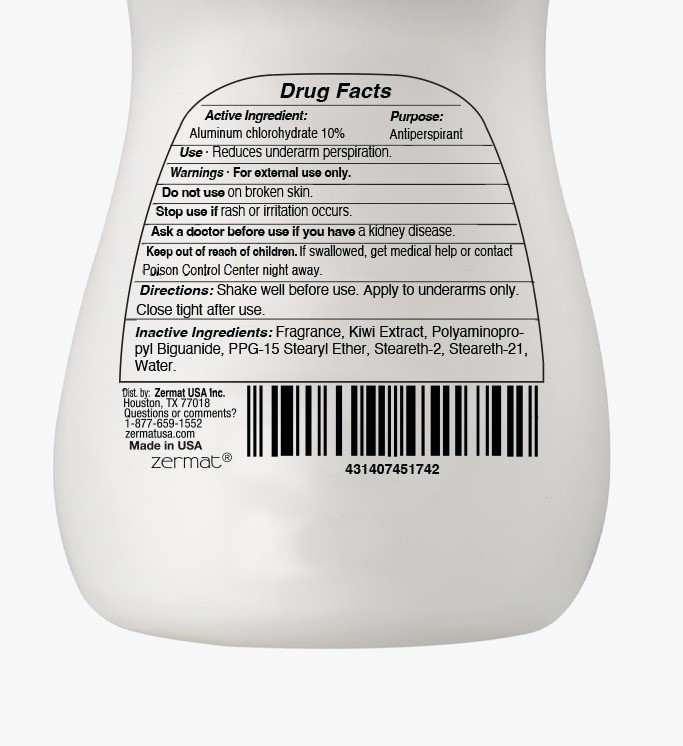 DRUG LABEL: KIWI ANTIPERSPIRANT DEODORANT ROLL-ON
NDC: 84178-009 | Form: CREAM
Manufacturer: Evi Labs
Category: otc | Type: HUMAN OTC DRUG LABEL
Date: 20260108

ACTIVE INGREDIENTS: ALUMINUM CHLOROHYDRATE 8 g/80 g
INACTIVE INGREDIENTS: PPG-15 STEARYL ETHER 3.2 g/80 g; STEARETH-2 3.2 g/80 g; STEARETH-21 1.8 g/80 g; POLYAMINOPROPYL BIGUANIDE 0.16 g/80 g; WATER 62 g/80 g

ZERMAT-KIWI ANTIPERSPIRANT DEODORANT ROLL-ON

Active Ingredient

Active Ingredient: Aluminum chlorohydrate 10%.

Purpose

Antiperspirant

Use

Reduces underarm perspiration

Warnings

For external use only

Do not use on broken skin

Stop use if rash or irritation occurs

Ask a doctor before use if you have a kidney disease.

Keep of reach of children. If swallowed, get medical help or contact a Poison Control Center night away.

INSTRUCTIONS FOR USE

Shake well before use. Apply to underarms only. Close tight after use.

Inactive Ingredients

Fragrance, Poly aminopropyl Biguanide, PPG-15 Stearyl Ether, Steareth-2, Steareth-21, Water, Glycerin/ Actinidia Chinensis Fruit Extract/Sodium Benzoate/ Potassium Sorbate (Fruit Ectract).

INDICATIONS & USAGE

Do not use on broken skin.

Stop use if rash or irritation occurs.

DIRECTIONS

SHAKE WELL BEFORE USE. APPLY TO UNDERARMS ONLY CLOSE TIGHT AFTER USE.

KEEP OUT OF REACH OF CHILDREN

Keep of reach of children. If swallowed, get medical help or contact

Poison Control Center night away.